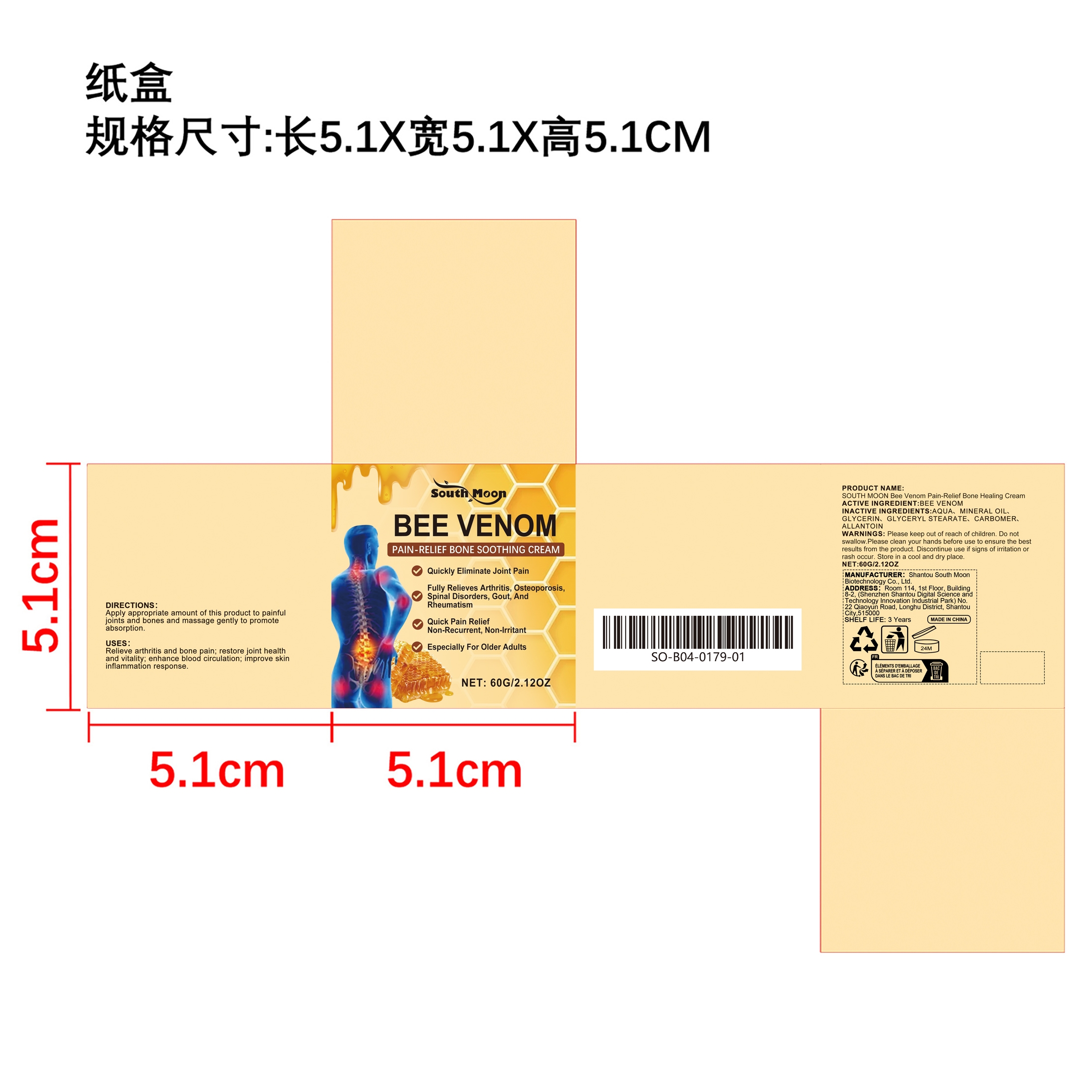 DRUG LABEL: SOUTH MOON Bee Venom Pain-Relief Bone Healing Cream
NDC: 84983-017 | Form: CREAM
Manufacturer: Shantou South Moon Biotechnology Co., Ltd.
Category: otc | Type: HUMAN OTC DRUG LABEL
Date: 20251127

ACTIVE INGREDIENTS: APIS MELLIFERA VENOM 0.012 mg/60 mg
INACTIVE INGREDIENTS: AQUA 52.056 mg/60 mg; GLYCERYL STEARATE 1.2 mg/60 mg; CARBOMER 0.12 mg/60 mg; ALLANTOIN 0.012 mg/60 mg; MINERAL OIL 4.8 mg/60 mg; GLYCERIN 1.8 mg/60 mg

ACTIVE INGREDIENT

APIS MELLIFERA VENOM

PURPOSE

Relieve arthritis and bone pain; restore joint health and vitality; enhance blood circulation; improve skin inflammation response.

WHEN USING

Apply appropriate amount of this product to painful joints and bones and massage gently to promote absorption.

WARNINGS

Please keep out of reach of children. Do not swallow.Please clean your hands before use to ensure the best results from the product. Discontinue use if signs of irritation or rash occur. Store in a cool and dry place.

KEEP OUT OF REACH OF CHILDREN

Please keep out of reach of children. Do not swallow.

DO NOT USE

Discontinue use if signs of irritation or rash occur.

STOP USE

Discontinue use if signs of irritation or rash occur.

STORAGE AND HANDLING

Store in a cool and dry place.

INACTIVE INGREDIENT

AQUA、MINERAL OIL、GLYCERIN、GLYCERYL STEARATE、CARBOMER、ALLANTOIN

DOSAGE AND ADMINISTRATION

Apply appropriate amount of this product to painful joints and bones and massage gently to promote absorption.

INDICATIONS AND USAGE

Apply appropriate amount of this product to painful joints and bones and massage gently to promote absorption.